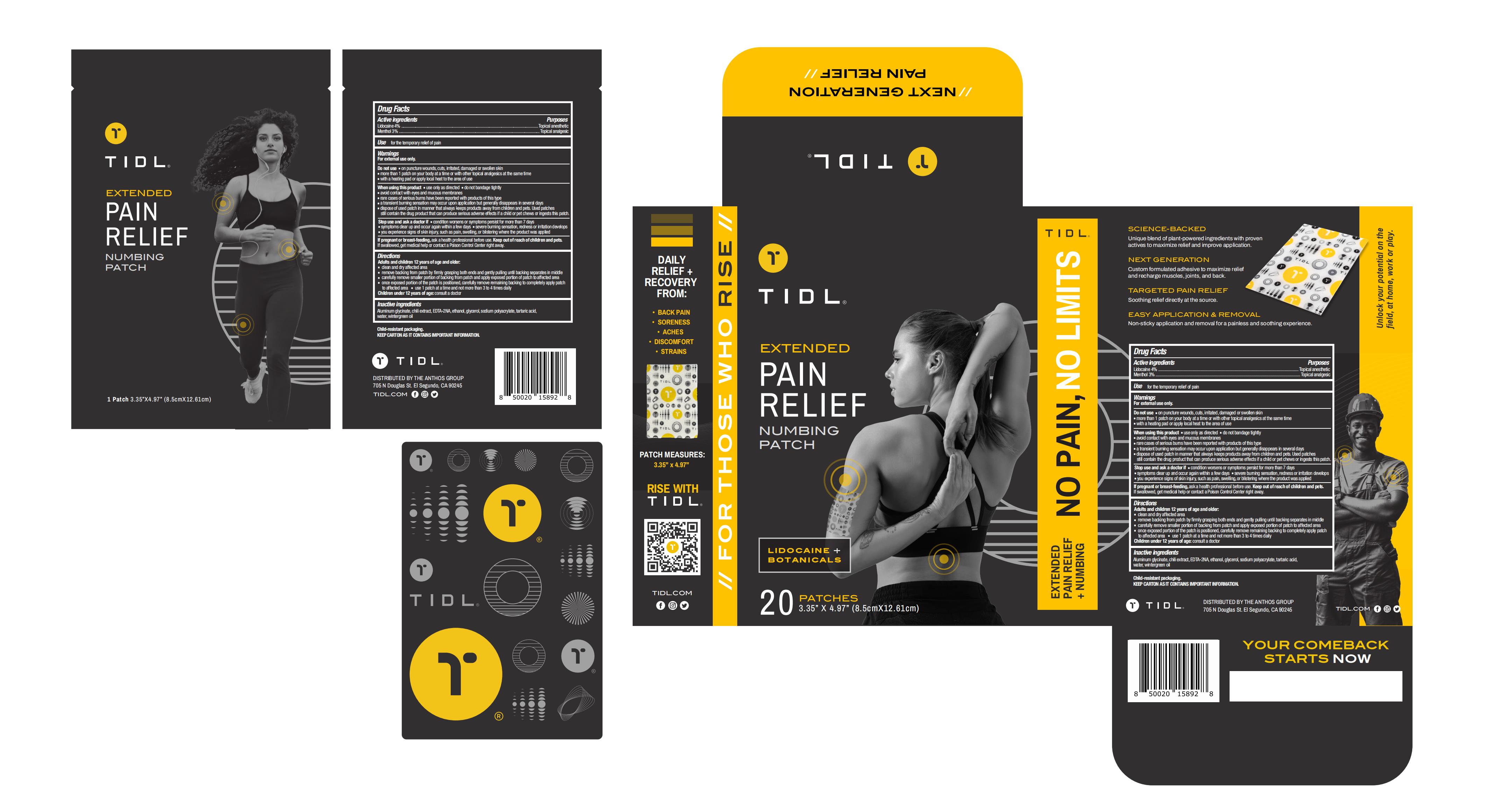 DRUG LABEL: Tidl Pain Relief Numbing Patch
NDC: 83822-003 | Form: PATCH
Manufacturer: Fuzhou Ayimong Trading Co., Ltd.
Category: otc | Type: HUMAN OTC DRUG LABEL
Date: 20240323

ACTIVE INGREDIENTS: MENTHOL 3 g/100 1; LIDOCAINE 4 g/100 1
INACTIVE INGREDIENTS: WATER; METHYL SALICYLATE; TARTARIC ACID; ALCOHOL; EDETIC ACID; DIHYDROXYALUMINUM AMINOACETATE ANHYDROUS; GLYCERIN; CAPSICUM; SODIUM POLYACRYLATE (2500000 MW)

83822-003

Active Ingredient

Lidocaine 4%
Menthol 3%

Purpose

Topical anesthetic

Use

for the temporary relief of pain

Warnings

For external use only

Do not use

·on puncture wounds,cuts,irritated,damaged or swollwn skin

·more than 1 patch on your body at a time or with other topical analgesics at the same time

·with a heating pad or apply local heat to the area of use

When Using

·use only as directed

·do not bandage tightly

·avoid contact with eyes and mucous membranes

·rare cases of serious burns have been reported with products of this type

·a transient burning sensation may occur upon application but generally disappears in several days

·dispose of used patch in manner that always keeps products away from children and pets.Used patches still contain the drug product that can produce serious adverse effects if a child or pet chews or ingests this patch.

Stop Use

·condition worsens or symptoms persist for more than 7 days
·symptoms clear up and occur again within a few days
·severe burning sensation,redness or irritation develops
·you experience signs of skin injury,such as pain,swelling,or blistering where the product was applied

Ask Doctor

·condition worsens or symptoms persist for more than 7 days
·symptoms clear up and occur again within a few days
·severe burning sensation,redness or irritation develops
·you experience signs of skin injury,such as pain,swelling,or blistering where the product was applied

Keep Oot Of Reach Of Children

If swallowed, get medical help or contact a poison control center right away.

Directions

Adults and children 12 years of age and older:
-clean and dry affected area
-remove backing from patch by firmly grasping both ends and gently pulling until backing seprarates in middle
-carefully remove smaller portion of backing from patch and apply exposed portion of patch to affected area
-once exposed portion of the patch is positioned,carefully remove remaining backing to completely apply patch
to affected area - use 1 patch at a time and not more than 3 to 4 times daily
Children under 12 years of age: consult a doctor

Inactive ingredients

Aluminum glycinate, chili extract, EDTA-2NA, ethanol, glycerol, sodium polyacrylate, tartaric acid,
water, wintergreen oil